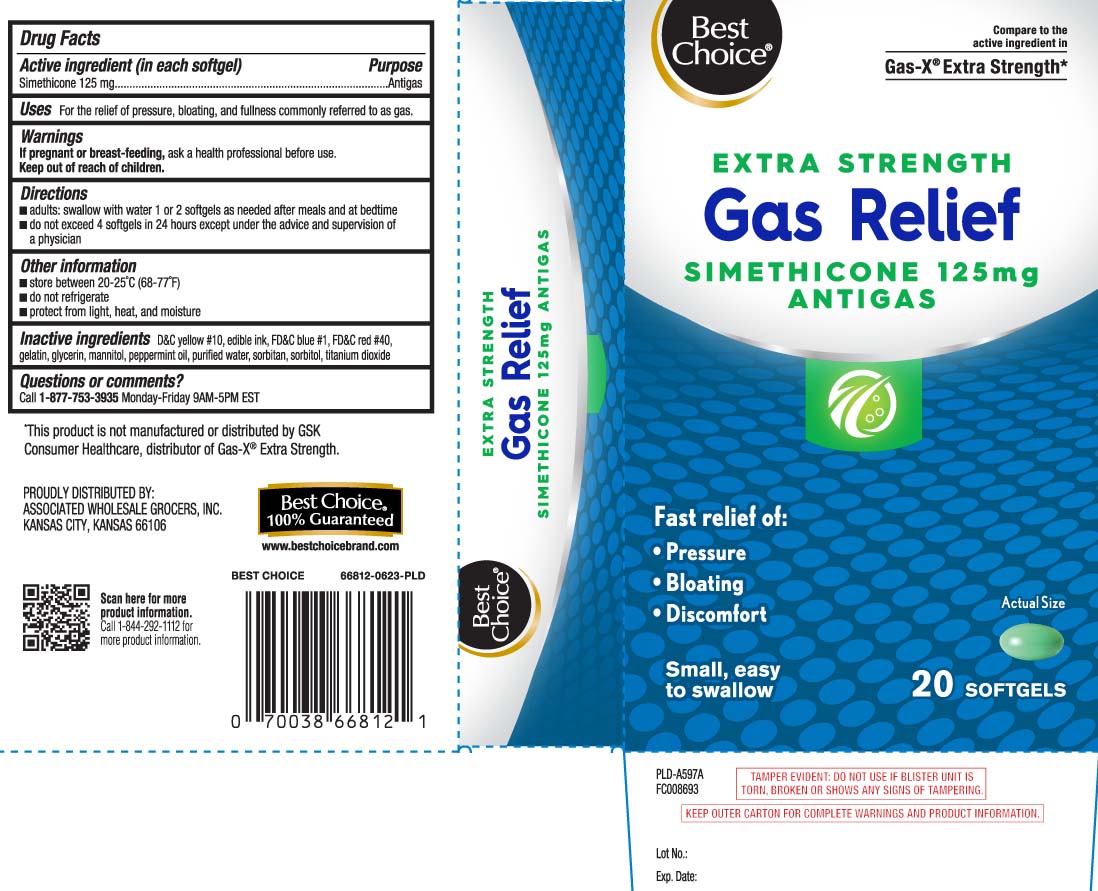 DRUG LABEL: Gas Relief
NDC: 63941-897 | Form: CAPSULE, LIQUID FILLED
Manufacturer: Best Choice  (Valu Merchandisers Company)
Category: otc | Type: HUMAN OTC DRUG LABEL
Date: 20251124

ACTIVE INGREDIENTS: DIMETHICONE 125 mg/1 1
INACTIVE INGREDIENTS: D&C YELLOW NO. 10; FD&C BLUE NO. 1; FD&C RED NO. 40; GELATIN; GLYCERIN; PEPPERMINT OIL; WATER; SORBITAN; SORBITOL; TITANIUM DIOXIDE; MANNITOL

Drug Facts

Active ingredient (in each softgel)

Simethicone 125 mg

Purpose

Antigas

Uses

for the relief of pressure, bloating, and fullness commonly referred to as gas.

Warnings

If pregnant or breast-feeding,

ask a health professional before use.

Directions

- adults: swallow with water 1 or 2 softgels as needed after meals and at bedtime
- do not exceed 4 softgels in 24 hours except under the advice and supervision of a physican

Other information

- store between 20-25°C (68-77°F)
- do not refrigerate
- protect from light, heat, and moisture

Inactive ingredients

D&C yellow #10, edible ink, FD&C blue #1, FD&C red #40, gelatin, glycerin, mannitol, peppermint oil, purified water, sorbitan, sorbitol, titanium dioxide

Questions or comments?

Call 1-877-753-3935 Monday-Friday 9am-5pm EST

Principal Display Panel

Compare to the active ingredient in Gas-X® Extra Strength*

EXTRA STRENGTH

Gas Relief

SIMETHICONE 125 mg

ANTIGAS

Fast Relief of:

- Pressure
- Bloating
- Discomfort

Small, easy

to swallow

SOFTGELS

*This product is not manufactured or distributed by GSK Consumer Healthcare, distributor of Gas-X® Extra Strength.

TAMPER EVIDENT: DO NOT USE IF BLISTER UNIT IS TORN, BROKEN OR SHOWS ANY SIGNS OF TAMPERING.

KEEP OUTER CARTON FOR COMPLETE WARNINGS AND PRODUCT INFORMATION.

PROUDLY DISTRIBUTED BY:

ASSOCIATED WHOLESALE GROCERS, INC.

KANSAS CITY, KANSAS 66106

Product Label

BEST CHOICE Extra Strength Gas Relief